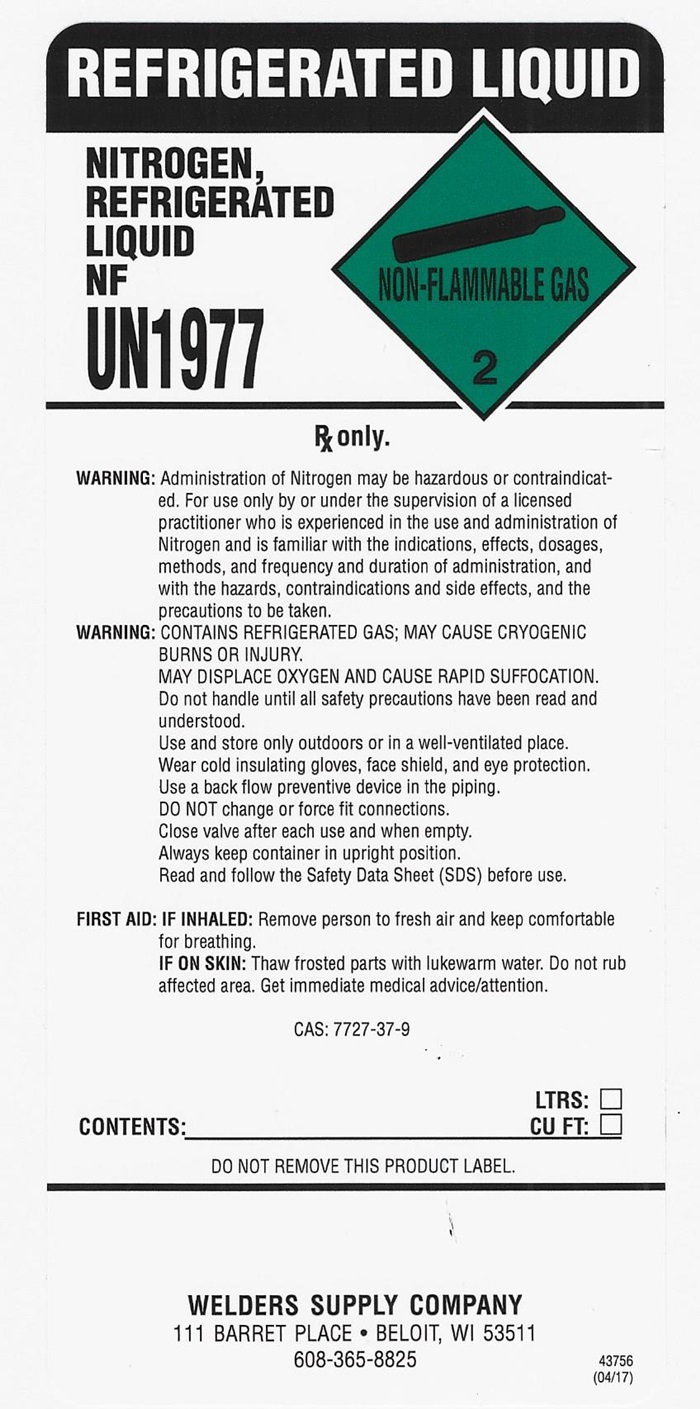 DRUG LABEL: NITROGEN
NDC: 11999-002 | Form: GAS
Manufacturer: Welders Supply Company
Category: prescription | Type: HUMAN PRESCRIPTION DRUG LABEL
Date: 20260106

ACTIVE INGREDIENTS: NITROGEN 990 mL/1 L

Nitrogen

NITROGEN N.F. REFRIGERATED LABEL

REFRIGERATED LIQUID

NITROGEN, REFRIGERATED LIQUID NF UN1977 NON-FLAMMABLE GAS 2

Rx only.

WARNING: Administration of Nitrogen may be hazardous or contraindicated. For use only by or under the supervision of a licensed practitioner who is experienced in the use and administration of Nitrogen and is familiar with the indications, effects, dosages, methods, and frequency and duration of administration, and with the hazards, contraindications, and side effects, and the precautions to be taken.

WARNING:CONTAINS REFRIGERATED GAS; MAY CAUSE CRYOGENIC BURNS OR INUURY. MAY DISPLACE OXYGEN AND CAUSE RAPID SUFFOCATION. Do not handle until all safety precautions have been read and understood. Use and store only outdoors or in a well-ventilated place. Wear cold insulating gloves, face shield, and eye protection. Use a back flow preventive device in the piping. DO NOT change or force fit connections. Close valve after each use and when empty. Always keep container in upright position. Read and follow the Safety Data Sheet (SDS) before use.

FIRST AID: IF INHALED:Remove person to fresh air and keep comfortable for breathing. IF ON SKIN: Thaw frosted parts with lukewarm water. Do not rub affected area. Get immediate medical advice/attention.

CAS: 7727-37-9

LTRS: ___

CONTENTS: ____________________ CU FT: ___

DO NOT REMOVE THIS PRODUCT LABEL.

WELDERS SUPPLY COMPANY

111 BARRETT PLACE • BELOIT, WI 53511

608-365-8825

43756

(04/17)